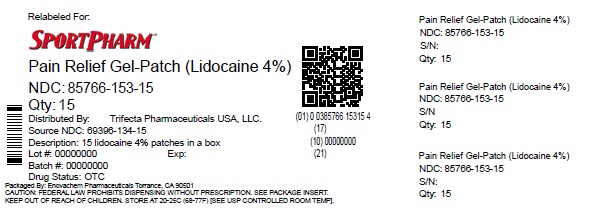 DRUG LABEL: Pain Relief Gel-Patch
NDC: 85766-153 | Form: PATCH
Manufacturer: Sportpharm LLC
Category: otc | Type: HUMAN OTC DRUG LABEL
Date: 20260206

ACTIVE INGREDIENTS: LIDOCAINE 4 g/100 g
INACTIVE INGREDIENTS: POLYACRYLIC ACID (8000 MW); POLYSORBATE 80; TARTARIC ACID; METHYLPARABEN; SODIUM POLYACRYLATE (8000 MW); TITANIUM DIOXIDE; WATER; GLYCERIN; PROPYLENE GLYCOL; KAOLIN; EDETATE SODIUM; POVIDONE K90; PROPYLPARABEN; DIHYDROXYALUMINUM AMINOACETATE

Globe Pain Relief Gel-Patch

Active Ingredient

Lidocaine 4%

Purpose

Topical Anesthetic

INDICATIONS AND USAGE

For temporary relief of pain

Warnings

For External Use Only

Stop use and ask a doctor

- Localized skin reaction occur, such as rash, itching, redness, irritation, pain, swelling and blistering
- Condition worsens
- Symptoms persist for more than 7 days
- Symptoms clear up and occur again within a few days

Keep out of the reach of children

If swallowed, get medical help or contact a Poison Control Center right away.

Do Not Use

- More than 1 patch at a time
- On wounds or damaged skin
- with a heating pad
- if you are allergic to any ingredients of this product

If Pregnant or Breast-Feeding

Ask a health professional before use

When Using this product

- Use only as directed
- Avoid contact with eyes, mucous membranes or rashes
- Do not bandage tightly

Directions

Adult and children 12 years of age and over:

- Clean and dry affected area
- Remove film from patch and apply to the skin
- Apply 1 patch at a time to affected area, not more than 3 to 4 times daily
- Remove patch from teh skin after at most 8-hour application
- Children under 12 years of age. Consult a doctor

Other information

- Store at controlled room temperature 68º-77ºF (20º-25ºC)
- Avoid storing product in direct sunlight
- Protect product from excessive moisture

Inactive Ingredients

Dihydroxyaluminum aminoacetate, Edetate disodium, Glycerin, Kaolin, Methylparaben, Polyacrylic acid, Polysorbate 80, Polyvinylpyrrolidone K90, Propylene glycol, propylparaben, sodium polyacrylate, tartaric acid, titanium dioxide, water.

Questions or Comments

Call 1-888-296-9067

Distributed by:

Sportpharm LLC

379 Van Ness Ave 1401,

Torrance, CA 90501

Relabeled by:

Enovachem PHARMACEUTICALS

Torrance, CA 90501